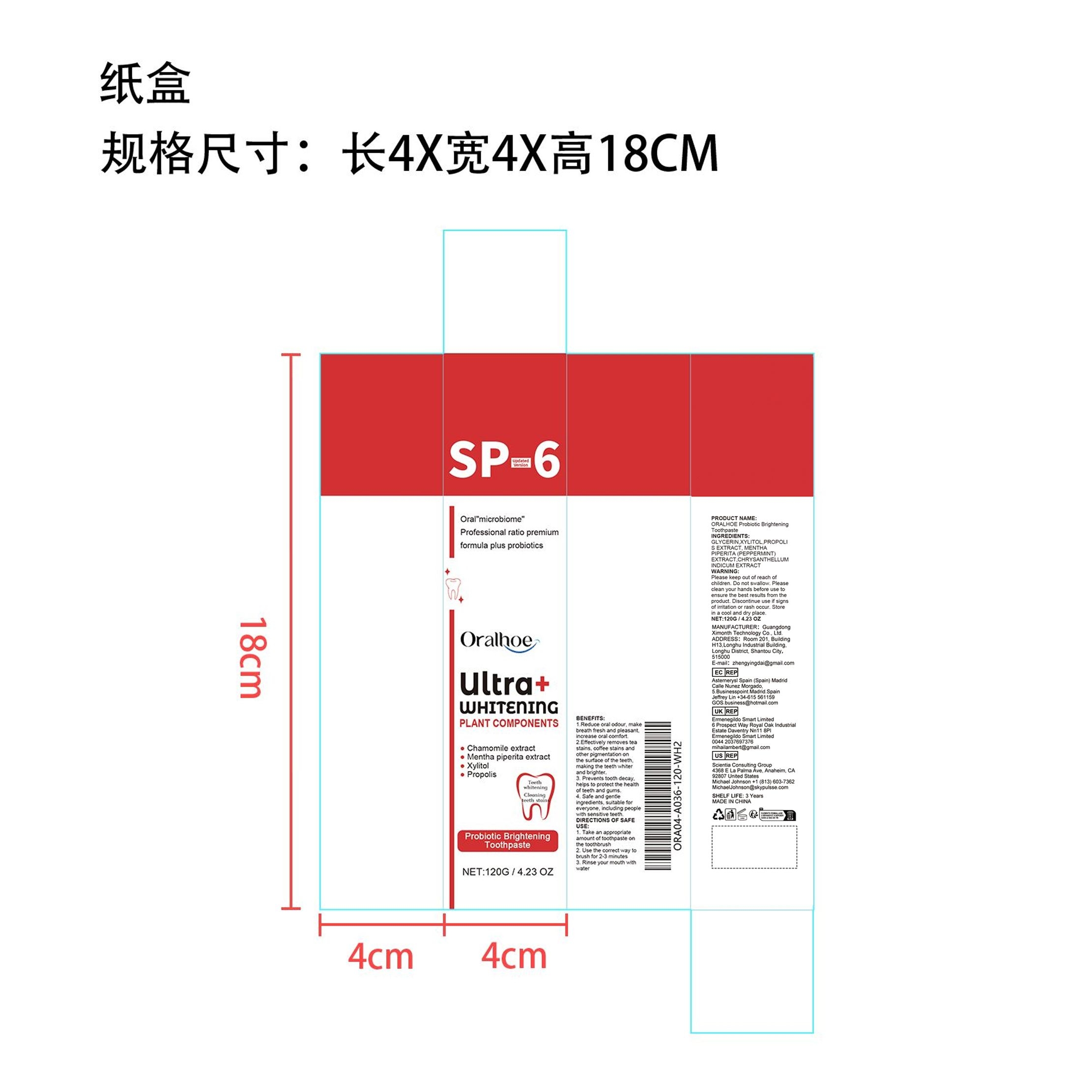 DRUG LABEL: ORALHOE Probiotic Brightening
NDC: 84660-036 | Form: CREAM
Manufacturer: Guangdong Ximonth Technology Co., Ltd.
Category: otc | Type: HUMAN OTC DRUG LABEL
Date: 20240926

ACTIVE INGREDIENTS: MENTHA X PIPERITA WHOLE 18 g/120 g; CHRYSANTHELLUM INDICUM TOP 12 g/120 g; XYLITOL 30 g/120 g; PROPOLIS WAX 24 g/120 g
INACTIVE INGREDIENTS: GLYCERIN 36 g/120 g

Active Ingredient(s)

XYLITOL、PROPOLIS EXTRACT、MENTHA PIPERITA (PEPPERMINT)EXTRACT、CHRYSANTHELLUM INDICUM EXTRACT

Purpose

1.Reduce oral odour, make breath fresh and pleasant, increase oral comfort.
2.Effectively removes tea stains, coffee stains and other pigmentation on the surface of the teeth, making the teeth whiter and brighter.
3. Prevents tooth decay, helps to protect the health of teeth and gums.
4. Safe and gentle ingredients, suitable for everyone, including people with sensitive teeth.

Use

1. Take an appropriate amount of toothpaste on the toothbrush
2. Use the correct way to brush for 2-3 minutes
3. Rinse your mouth with water

Warnings

Please keep out of reach of children.Do not swallow.Please clean your hands before use to ensure the best results from the product.Discontinue use if signs of irritation or rash occur.Store in a cool and dry place.

Do not use

Discontinue use if signs of irritation or rash occur.

STOP USE

Discontinue use if signs of irritation or rash occur.

KEEP OUT OF REACH OF CHILDREN

Please keep out of reach of children. Do not swallow.

STORAGE AND HANDLING

Avoid freezing and excessive heat above 40C (104F) ）
Store in a cool and dry place.

INACTIVE INGREDIENT

GLYCERIN